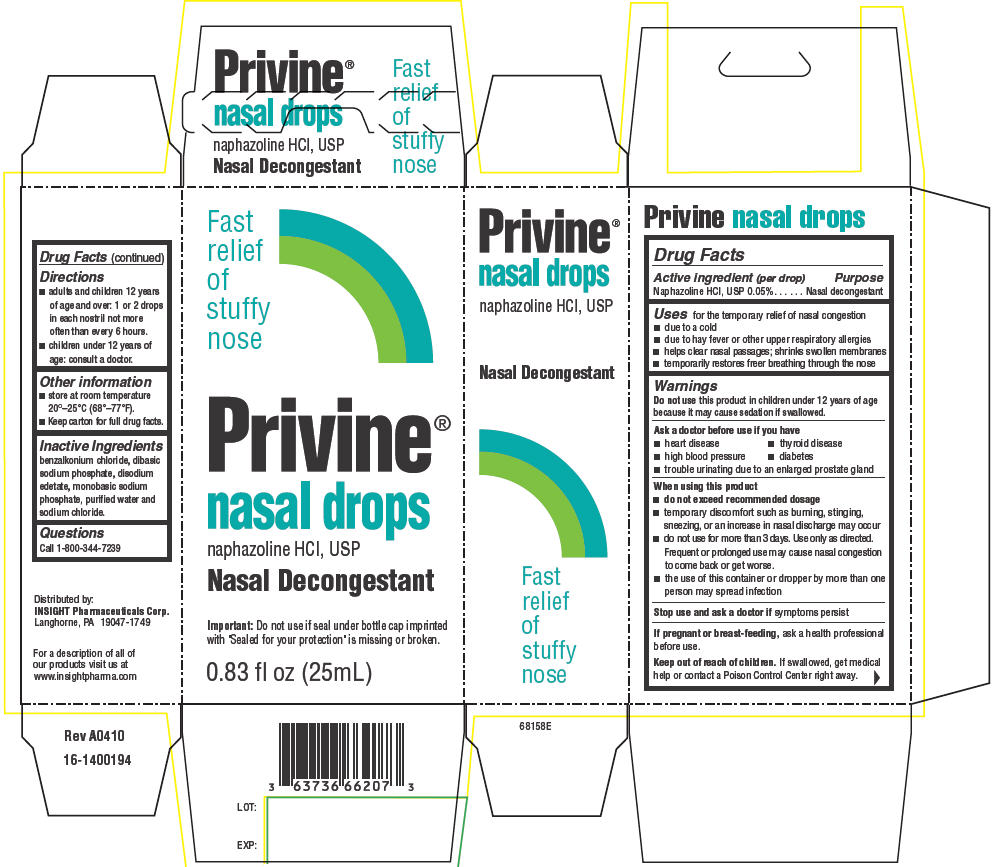 DRUG LABEL: Privine
NDC: 63736-663 | Form: SUSPENSION/ DROPS
Manufacturer: Insight Pharmaceuticals LLC
Category: otc | Type: HUMAN OTC DRUG LABEL
Date: 20110131

ACTIVE INGREDIENTS: Naphazoline Hydrochloride 0.125 mL/25 mL
INACTIVE INGREDIENTS: benzalkonium chloride; sodium phosphate, dibasic; edetate disodium; sodium phosphate, monobasic; water; sodium chloride

Privine®
nasal drops

Drug Facts

Active ingredient (per drop)

Naphazoline HCl, USP 0.05%

Purpose

Nasal decongestant

Uses

for the temporary relief of nasal congestion

- due to a cold
- due to hay fever or other upper respiratory allergies
- helps clear nasal passages; shrinks swollen membranes
- temporarily restores freer breathing through the nose

Warnings

Do not use this product in children under 12 years of age because it may cause sedation if swallowed.

Ask a doctor before use if you have

- heart disease
- thyroid disease
- high blood pressure
- diabetes
- trouble urinating due to an enlarged prostate gland

When using this product

- do not exceed recommended dosage
- temporary discomfort such as burning, stinging, sneezing, or an increase in nasal discharge may occur
- do not use for more than 3 days. Use only as directed. Frequent or prolonged use may cause nasal congestion to come back or get worse.
- the use of this container or dropper by more than one person may spread infection

Stop use and ask a doctor if symptoms persist

PREGNANCY OR BREAST FEEDING

If pregnant or breast-feeding, ask a health professional before use.

Keep out of reach of children. If swallowed, get medical help or contact a Poison Control Center right away.

Directions

- adults and children 12 years of age and over: 1 or 2 drops in each nostril not more often than every 6 hours.
- children under 12 years of age: consult a doctor.

Other information

- store at room temperature 20°–25°C (68°–77°F).
- Keep carton for full drug facts.

Inactive Ingredients

benzalkonium chloride, dibasic sodium phosphate, disodium edetate, monobasic sodium phosphate, purified water and sodium chloride.

Questions

Call 1-800-344-7239

Distributed by:
INSIGHT Pharmaceuticals Corp.
Langhorne, PA 19047-1749

PRINCIPAL DISPLAY PANEL - 25 mL Drops Carton

Fast
relief
of
stuffy
nose

Privine®
nasal drops
naphazoline HCl, USP
Nasal Decongestant

Important: Do not use if seal under bottle cap imprinted
with "Sealed for your protection" is missing or broken.

0.83 fl oz (25mL)